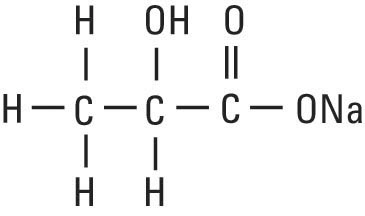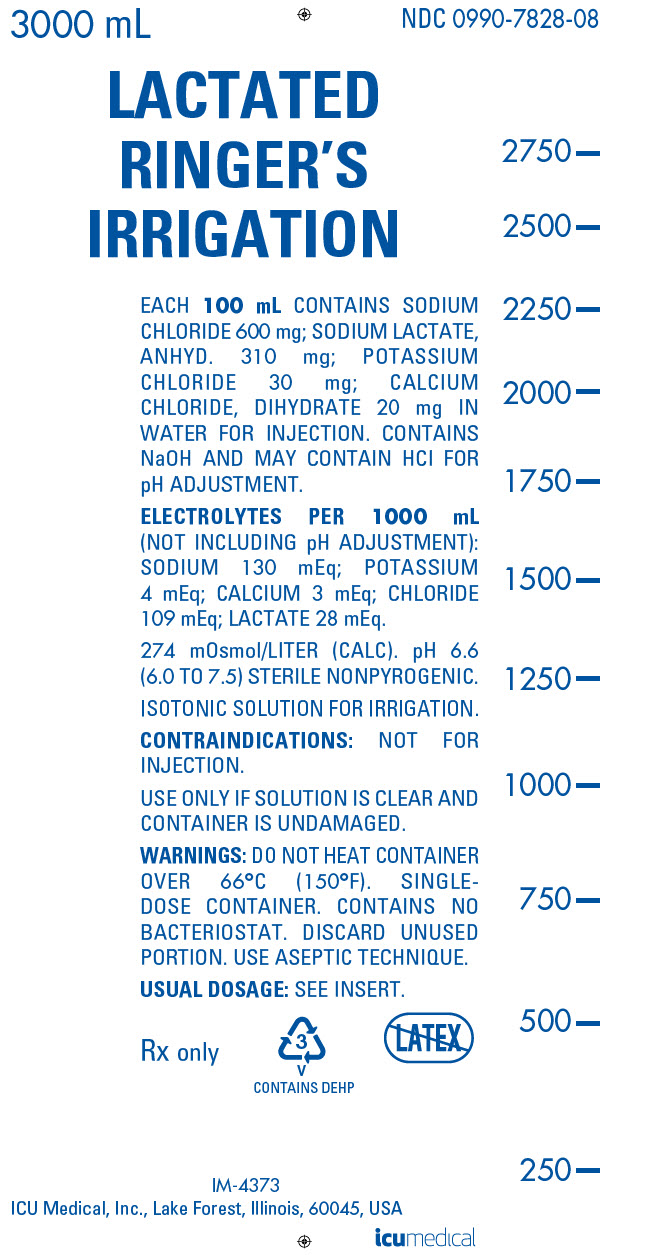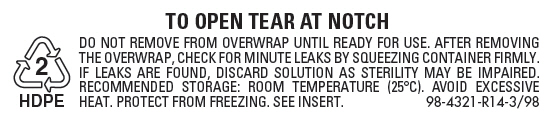 DRUG LABEL: Lactated Ringers
NDC: 0990-7828 | Form: IRRIGANT
Manufacturer: ICU Medical Inc.
Category: prescription | Type: HUMAN PRESCRIPTION DRUG LABEL
Date: 20251023

ACTIVE INGREDIENTS: SODIUM CHLORIDE 600 mg/100 mL; SODIUM LACTATE 310 mg/100 mL; POTASSIUM CHLORIDE 30 mg/100 mL; CALCIUM CHLORIDE 20 mg/100 mL
INACTIVE INGREDIENTS: WATER; SODIUM HYDROXIDE; HYDROCHLORIC ACID

LACTATED RINGER’S IRRIGATION

FOR ALL GENERAL IRRIGATION, WASHING AND RINSING PURPOSES

Not For Injection By Usual Parenteral Routes

Flexible Irrigation Container

Rx Only

DESCRIPTION

Lactated Ringer’s Irrigation is a sterile, nonpyrogenic solution of electrolytes in water for injection intended only for sterile irrigation, washing and rinsing purposes. The composition is based on a modification of the injectable formula originally known as Hartmann’s Solution.

Each 100 mL of Lactated Ringer’s Irrigation contains: Sodium chloride 600 mg; sodium lactate, anhydrous 310 mg; potassium chloride 30 mg; calcium chloride, dihydrate 20 mg. The pH is 6.6 (6.0 — 7.5). The solution is isotonic (274 mOsmol/liter, calc.) and has the following electrolyte content (mEq/liter): Sodium (Na^+) 130; potassium (K^+) 4; calcium (Ca^++) 3; chloride (Cl^−) 109 and lactate (CH3CH(OH)COO^−) 28. Contains sodium hydroxide and may contain hydrochloric acid for pH adjustment.

The solution contains no bacteriostat, antimicrobial agent or added buffer and is intended only for use as a single-dose or short procedure irrigation. When smaller volumes are required, the unused portion should be discarded. Lactated Ringer’s Irrigation may be classified as a sterile irrigant, wash, rinse and pharmaceutical vehicle.

Calcium Chloride, USP is chemically designated calcium chloride, dihydrate (CaCl2 • 2H2O), white fragments or granules freely soluble in water.

Potassium Chloride, USP is chemically designated KCl, a white granular powder freely soluble in water.

Sodium Chloride, USP is chemically designated NaCl, a white crystalline powder freely soluble in water.

Sodium Lactate, USP is chemically designated C3H5NaO3, a 60% aqueous solution miscible in water. It has the following structural formula:

Water for Injection, USP is chemically designated H2O.

The flexible plastic container is fabricated from a specially formulated polyvinylchloride. Water can permeate from inside the container into the overwrap but not in amounts sufficient to affect the solution significantly. Solutions inside the plastic container also can leach out certain of its chemical components in very small amounts before the expiration period is attained. However, the safety of the plastic has been confirmed by tests in animals according to USP biological standards for plastic containers.

CLINICAL PHARMACOLOGY

Lactated Ringer’s Irrigation exerts a mechanical cleansing action for sterile irrigation of body cavities, tissues or wounds, indwelling urethral catheters and surgical drainage tubes, and for washing, rinsing or soaking surgical dressings, instruments and laboratory specimens. It also serves as a vehicle for drugs used for irrigation or other pharmaceutical preparations.

Lactated Ringer’s Irrigation provides an isotonic irrigation with the same ionic constituents as Lactated Ringer’s Injection, USP, a modification of Hartmann’s Solution.

Lactated Ringer’s Irrigation is considered generally compatible with living tissues and organs.

Calcium chloride in water dissociates to provide calcium (Ca^++) and chloride (Cl^−) ions. They are normal constituents of the body fluids and are dependent on various physiologic mechanisms for maintenance of balance between intake and output. Approximately 80% of body calcium is excreted in the feces as insoluble salts; urinary excretion accounts for the remaining 20%.

Potassium chloride in water dissociates to provide potassium (K^+) and chloride (Cl^−) ions. Potassium is the chief cation of body cells (160 mEq/liter of intracellular water). It is found in low concentration in plasma and extracellular fluids (3.5 to 5.0 mEq/liter in a healthy adult). Potassium plays an important role in electrolyte balance.

Normally about 80 to 90% of the potassium intake is excreted in the urine; the remainder in the stools and to a small extent, in the perspiration. The kidney does not conserve potassium well so that during fasting or in patients on a potassium-free diet, potassium loss from the body continues resulting in potassium depletion.

Sodium chloride in water dissociates to provide sodium (Na^+) and chloride (Cl^−) ions. Sodium (Na^+) is the principal cation of the extracellular fluid and plays a large part in the therapy of fluid and electrolyte disturbances. Chloride (Cl^−) has an integral role in buffering action when oxygen and carbon dioxide exchange occurs in the red blood cells. The distribution and excretion of sodium (Na+) and chloride (Cl^−) are largely under the control of the kidney which maintains a balance between intake and output.

Sodium lactate in water dissociates to provide sodium (Na^+) and lactate (C3H5O3^–) ions. The lactate anion provides an alkalizing effect resulting from simultaneous removal by the liver of lactate and hydrogen ions. In the liver, the lactate is metabolized to glycogen which is ultimately converted to carbon dioxide and water by oxidative metabolism.

The lactate anion acts as a source (alternate) of bicarbonate when normal production and utilization of lactic acid is not impaired as a result of disordered lactate metabolism. Since metabolic conversion is dependent on the integrity of cellular oxidative processes, lactate may be inadequate or ineffective as a source of bicarbonate in patients suffering from acidosis associated with shock or other disorders involving reduced perfusion of body tissues. When oxidative activity is intact, one to two hours time is required for metabolism of lactate.

Water is an essential constituent of all body tissues and accounts for approximately 70% of total body weight. Average normal adult daily requirement ranges from two to three liters (1.0 to 1.5 liters each for insensible water loss by perspiration and urine production).

Water balance is maintained by various regulatory mechanisms. Water distribution depends primarily on the concentration of electrolytes in the body compartments and sodium (Na^+) plays a major role in maintaining physiologic equilibrium.

INDICATIONS AND USAGE

Lactated Ringer’s Irrigation is indicated for all general irrigation, washing and rinsing purposes which permit use of a sterile, nonpyrogenic electrolyte solution.

CONTRAINDICATIONS

NOT FOR INJECTION BY USUAL PARENTERAL ROUTES.

An electrolyte solution should not be used for irrigation during electrosurgical procedures.

WARNINGS

FOR IRRIGATION ONLY. NOT FOR INJECTION.

Irrigating fluids have been demonstrated to enter the systemic circulation in relatively large volumes; thus this irrigation must be regarded as a systemic drug. Absorption of large amounts can cause fluid and/or solute overloading resulting in dilution of serum electrolyte concentrations, overhydration, congested states or pulmonary edema.

The risk of dilutional states is inversely proportional to the electrolyte concentrations of administered parenteral solutions. The risk of solute overload causing congested states with peripheral and pulmonary edema is directly proportional to the electrolyte concentrations of such solutions.

Do not heat container over 66°C (150°F).

PRECAUTIONS

Do not use for irrigation that may result in absorption into the blood.

Caution should be observed when the solution is used for continuous irrigation or allowed to “dwell” inside body cavities because of possible absorption into the blood stream and the production of circulatory overload.

Aseptic technique is essential with the use of sterile solutions for irrigation of body cavities, wounds and urethral catheters or for wetting dressings that come in contact with body tissues.

The flexible container is designed for use with nonvented irrigation sets. When used for irrigation via irrigation equipment, the administration set should be attached promptly. Unused portions should be discarded and a fresh container of appropriate size used for the start-up of each cycle or repeat procedure. For repeated irrigations of urethral catheters, a separate container should be used for each patient.

Do not administer unless solution is clear and container is undamaged. Discard unused portion.

Pregnancy Category C.

Animal reproduction studies have not been conducted with Lactated Ringer’s Irrigation. It is also not known whether it can cause fetal harm when administered to a pregnant woman or can affect reproduction capacity. It should be given to a pregnant woman only if clearly needed.

Pediatric Use:

The safety and effectiveness of Lactated Ringer’s Irrigation have not been established. Its limited use in pediatric patients has been inadequate to fully define proper dosage and limitations for use.

ADVERSE REACTIONS

Possible adverse effects arising from the irrigation of body cavities, tissues, or indwelling catheters and tubes are usually avoidable when proper procedures are followed. Displaced catheters or drainage tubes can lead to irrigation or infiltration of unintended structures or cavities. Excessive volume or pressure during irrigation of closed cavities may cause undue distension or disruption of tissues. Accidental contamination from careless technique may transmit infection.

Should any adverse reaction occur, discontinue the irrigant, evaluate the patient, institute appropriate therapeutic countermeasures and save the remainder of the fluid for examination if deemed necessary.

OVERDOSAGE

In the event of overhydration or solute overload, re-evaluate the patient and institute appropriate corrective measures. (See WARNINGS, PRECAUTIONS and ADVERSE REACTIONS.)

DOSAGE AND ADMINISTRATION

The dose is dependent upon the capacity or surface area of the structure to be irrigated and the nature of the procedure. When used as a vehicle for other drugs, the manufacturer’s recommendations should be followed.

Tear at notch and along dotted line and remove container. Some opacity of the plastic due to moisture absorption during the sterilization process may be observed. This is normal and does not affect the solution quality or safety. The opacity will diminish gradually.

Drug Interactions

Additives may be incompatible. Consult with pharmacist, if available. When introducing additives, use aseptic technique, mix thoroughly and do not store.

Parenteral drug products should be inspected visually for particulate matter and discoloration prior to administration, whenever solution container permits. (See PRECAUTIONS.)

HOW SUPPLIED

Lactated Ringer’s Irrigation is supplied in single-dose 3000 mL flexible irrigation containers (NDC No. 0409–7828–08 / 0990-7828-08).

ICU Medical is transitioning NDC codes from the "0409" to a "0990" labeler code. Both NDC codes are expected to be in the market for a period of time.

Store at 20 to 25°C (68 to 77°F). [See USP Controlled Room Temperature.] Protect from freezing.

Revised: June 2018

EN-4659

ICU Medical, Inc., Lake Forest, Illinois 60045 USA

PRINCIPAL DISPLAY PANEL - 3000 mL Bag Label

3000 mL
NDC 0990-7828-08

LACTATED
RINGER'S
IRRIGATION

EACH 100 mL CONTAINS SODIUM
CHLORIDE 600 mg; SODIUM LACTATE,
ANHYD. 310 mg; POTASSIUM
CHLORIDE 30 mg; CALCIUM
CHLORIDE, DIHYDRATE 20 mg IN
WATER FOR INJECTION. CONTAINS
NaOH AND MAY CONTAIN HCl FOR
pH ADJUSTMENT.

ELECTROLYTES PER 1000 mL
(NOT INCLUDING pH ADJUSTMENT):
SODIUM 130 mEq; POTASSIUM
4 mEq; CALCIUM 3 mEq; CHLORIDE
109 mEq; LACTATE 28 mEq.

274 mOsmol/LITER (CALC). pH 6.6
(6.0 TO 7.5) STERILE NONPYROGENIC.

ISOTONIC SOLUTION FOR IRRIGATION.

CONTRAINDICATIONS: NOT FOR
INJECTION.

USE ONLY IF SOLUTION IS CLEAR AND
CONTAINER IS UNDAMAGED.

WARNINGS: DO NOT HEAT CONTAINER
OVER 66°C (150°F). SINGLE-
DOSE CONTAINER. CONTAINS NO
BACTERIOSTAT. DISCARD UNUSED
PORTION. USE ASEPTIC TECHNIQUE.

USUAL DOSAGE: SEE INSERT.

Rx only

3
V
CONTAINS DEHP

IM-4373

ICU Medical, Inc., Lake Forest, Illinois, 60045, USA

icumedical

PRINCIPAL DISPLAY PANEL - Pouch Label

TO OPEN TEAR AT NOTCH

2
HDPE

DO NOT REMOVE FROM OVERWRAP UNTIL READY FOR USE. AFTER REMOVING
THE OVERWRAP, CHECK FOR MINUTE LEAKS BY SQUEEZING CONTAINER FIRMLY.
IF LEAKS ARE FOUND, DISCARD SOLUTION AS STERILITY MAY BE IMPAIRED.
RECOMMENDED STORAGE: ROOM TEMPERATURE (25°C). AVOID EXCESSIVE
HEAT. PROTECT FROM FREEZING. SEE INSERT.
98-4321-R14-3/98